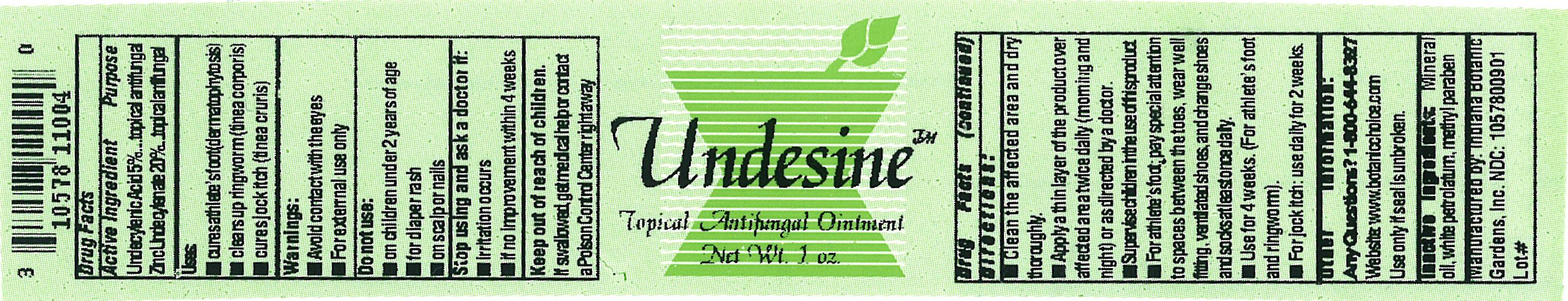 DRUG LABEL: Undesine
NDC: 10578-009 | Form: OINTMENT
Manufacturer: Indiana Botanic Gardens
Category: otc | Type: HUMAN OTC DRUG LABEL
Date: 20101201

ACTIVE INGREDIENTS: UNDECYLENIC ACID 5 g/100 g; ZINC UNDECYLENATE 20 g/100 g
INACTIVE INGREDIENTS: LIGHT MINERAL OIL; PETROLATUM; METHYLPARABEN

Undesine

Active Ingredient

Undecylenic acid 5%

Zinc undecylenate 20%

Purpose

topical antifungal

topical antifungal

Uses:

- cures athletes foot (dermatophytosis)
- clears up ringworm (tinea corporis)
- cures jock itch (tinea cruris)

Warnings: For external use only.

Avoid contact with the eyes.

Do not use:

- on children under 2 years of age
- for diaper rash
- on scalp or nails

Stop using and ask a doctor if

- irritation occurs
- if no improvement within 4 weeks

Keep out of reach of children. If swallowed, get medical help or contact a Poison Control Center right away.

Directions:

- clean the affected area and dry thoroughly
- apply a thin layer of the product over affected area twice daily (morning and night) or as directed by a doctor
- supervise children in the use of this product
- For athlete's foot: pay special attention to spaces between the toes, wear well fitting, ventilated shoes, and change shoes and socks at least once daily
- use for 4 weeks. (for athlete's foot and ringworm)
- for jock itch: use daily for 2 weeks

Other information:

To reorder call: 1-800-644-8327

website: www.botanicchoice.com

Use only of seal is unbroken

Manufactured by: Indiana Botanic Gardens, Inc.

NDC# 1057800901

INACTIVE INGREDIENT

Inactive ingredients: light mineral oil, white petrolatum, methylparaben